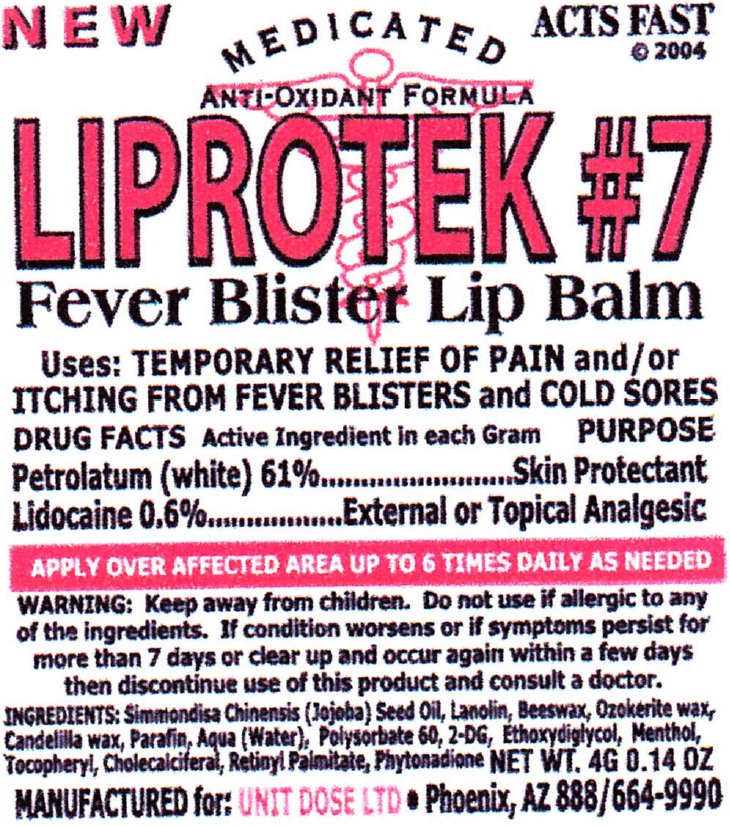 DRUG LABEL: Liprotek
NDC: 67194-017 | Form: OINTMENT
Manufacturer: Unit Dose, Ltd.
Category: otc | Type: HUMAN OTC DRUG LABEL
Date: 20231019

ACTIVE INGREDIENTS: PETROLATUM 610 mg/1 g; LIDOCAINE 6 mg/1 g
INACTIVE INGREDIENTS: JOJOBA OIL; LANOLIN; YELLOW WAX; CERESIN; CANDELILLA WAX; PARAFFIN; WATER; POLYSORBATE 60; 2-DEOXYGLUCOSE; DIETHYLENE GLYCOL MONOETHYL ETHER; MENTHOL; CHOLECALCIFEROL; VITAMIN A PALMITATE; PHYTONADIONE

Liprotek

Uses:

TEMPORARY RELIEF OF PAIN and/or ITCHING FROM FEVER BLISTERS and COLD SORES

Active Ingredient

Petrolatum (white) 61%

Lidocaine 0.6%

PURPOSE

Skin Protectant

External or Topical Analgesic

Uses:

TEMPORARY RELIEF OF PAIN AND/OR ITCHING FROM FEVER BLISTERS AND COLD SORES

WARNING:

Do not use

if allergic tp any of the ingredients. If condition worsens or if symptoms persist for more than 7 days or clear up and occur again within a few days then discontinue use of this product and cunsult a doctor.

INGREDIENTS:

Simmondisa Chinensis (Jojoba) Seed Oil, Lanolin, Beeswax, Ozokerite wax, Candelilla wax, Parafin, Aqua (Water), Polysorbate 60, 2-DG, Ethoxydiglycol, Menthol, Tocopheryl, Cholecalciferal, Retinyl Palmitate, Phytonadione